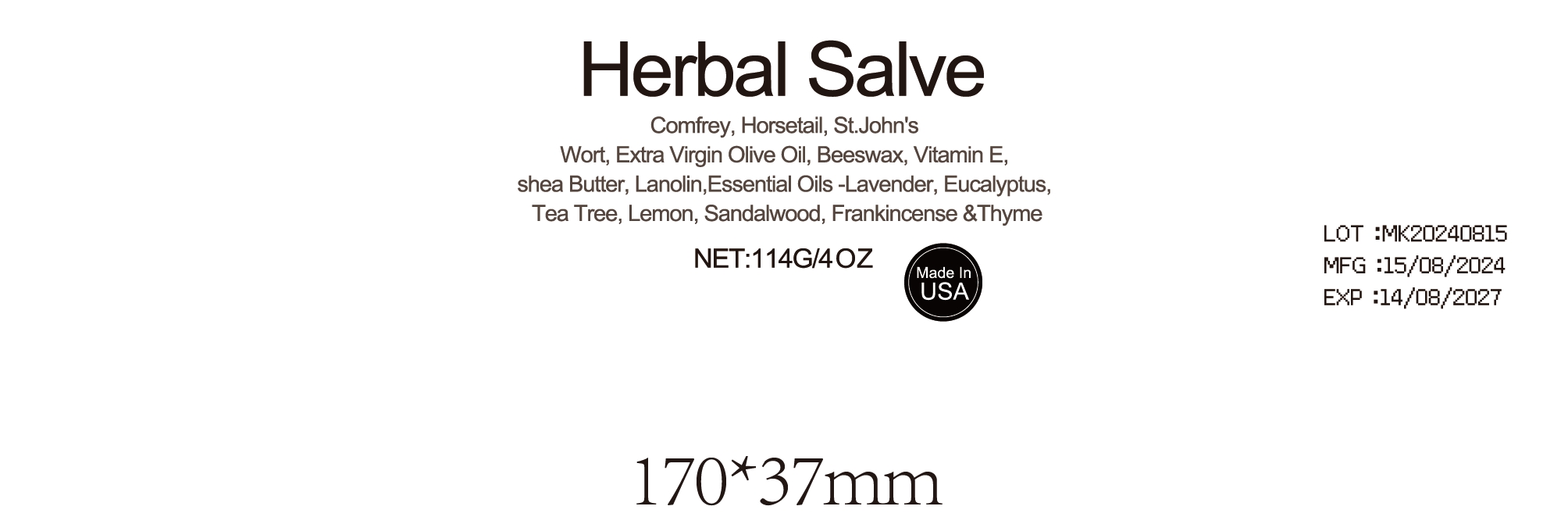 DRUG LABEL: Herbal Salve
NDC: 84732-918 | Form: CREAM
Manufacturer: Dongguan Haiyi Technology Co.,Ltd.
Category: otc | Type: HUMAN OTC DRUG LABEL
Date: 20240918

ACTIVE INGREDIENTS: SYMPHYTUM OFFICINALE WHOLE 1 g/100 g
INACTIVE INGREDIENTS: EQUISETUM ARVENSE WHOLE; BUTYROSPERMUM PARKII (SHEA) BUTTER UNSAPONIFIABLES; OLEA EUROPAEA (OLIVE) OIL UNSAPONIFIABLES; PEG-8 BEESWAX; HYPERICUM PERFORATUM; LAVANDULA ANGUSTIFOLIA FLOWERING TOP; TOCOPHEROL; LANOLIN; EUCALYPTUS GLOBULUS LEAF

Active ingredient

Symphytum Officinale Extract

Inactive ingredient

Equisetum Arvense Extract

Hypericum Perforatum Extract

Olea Europaea (Olive) Fruit Oil

Beeswax·Butyrospermum Parkii (Shea) Butter

Lanolin·Lavandula Angustifolia (Lavender) Oil

Eucalyptus Globulus Leaf Oil

Tocopherol

Purpose section

Composed of a variety of natural herbal ingredients

Warning

For externaluse only. Keep out of reach of children. Avoid direct contact with eyes.Discontinueuse ifirritation occurs.storein a cool and dry place.

stop use

if have the severe allergic reaction stop to use

not use

Pregnant women or severe skin diseases not to use

OUT OF CHILDREN

KEEP THE PRODUCT OUT OF REACH OF CHILDREN to

HOW TO USE

Apply twice a day

Dosage

5ml once